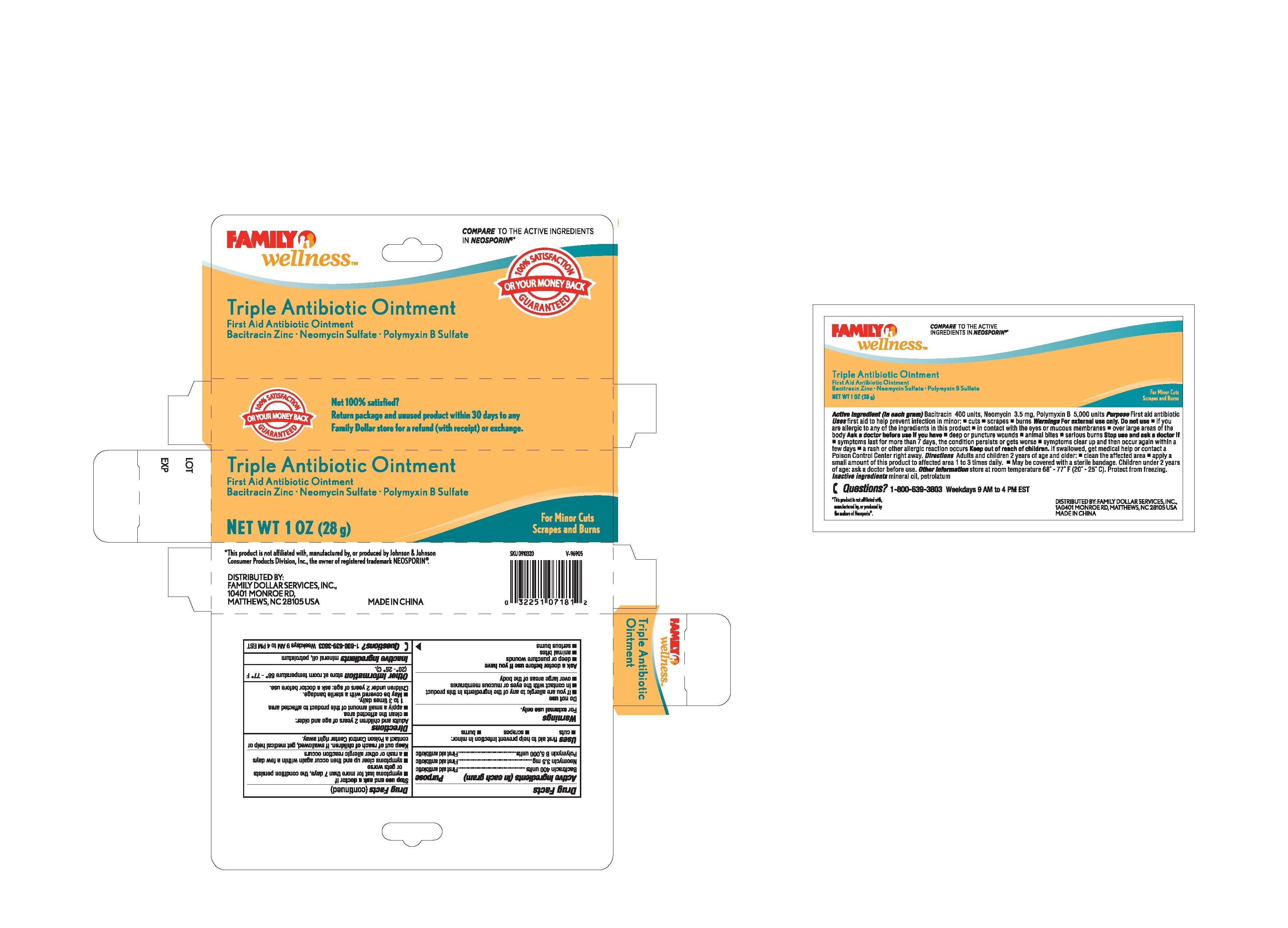 DRUG LABEL: Family Wellness
                
NDC: 55621-009 | Form: OINTMENT
Manufacturer: Zhejiang Jingwei Pharmaceutical Co., Ltd.
Category: otc | Type: HUMAN OTC DRUG LABEL
Date: 20130731

ACTIVE INGREDIENTS: BACITRACIN .41 g/100 g; NEOMYCIN .0035 g/100 g; POLYMYXIN B .52 g/100 g
INACTIVE INGREDIENTS: MINERAL OIL; PETROLATUM

Drug Facts

Inactive Ingredients mineral oil, petrolatum

Active Ingredient (in each gram)

Bacitracin 400 units

Neomycin 3.5 mg

Polymyxcin B 5,000 units

Purpose

First aid antibiotic

Keep out of reach of children. If swallowed, get medical help or contact a Poison Control Center right away.

INDICATIONS AND USAGE

Uses first aid to help prevent infection in minor:

-cuts

-scrapes

-burns

Warnings For external use only

Directions

adults and children 2 years of age and older:

-clean the affected area

-apply a small amount of this product to affected area 1 to 3 times daily

-may be covered with a sterile bandage

Children under 2 years of age: ask a doctor before use

Stop use and ask a doctor if

-symptoms last for more than 7 days, the condition persists or gets worse

-symptoms clear up and then occur again within a few days

-a rash or other allergic reaction occurs

Ask a doctor before use if you have

deep or puncture wounds

animal bites

serious burns